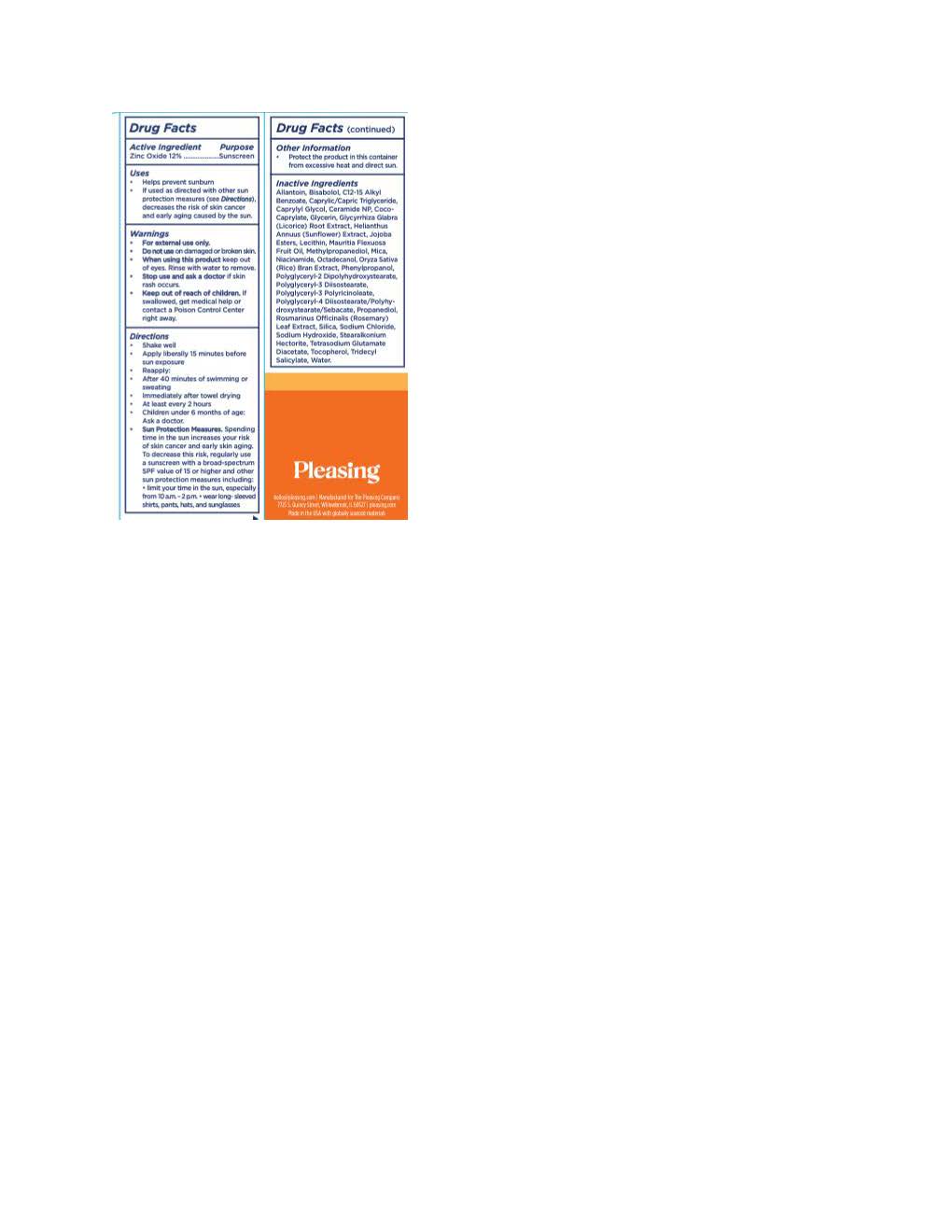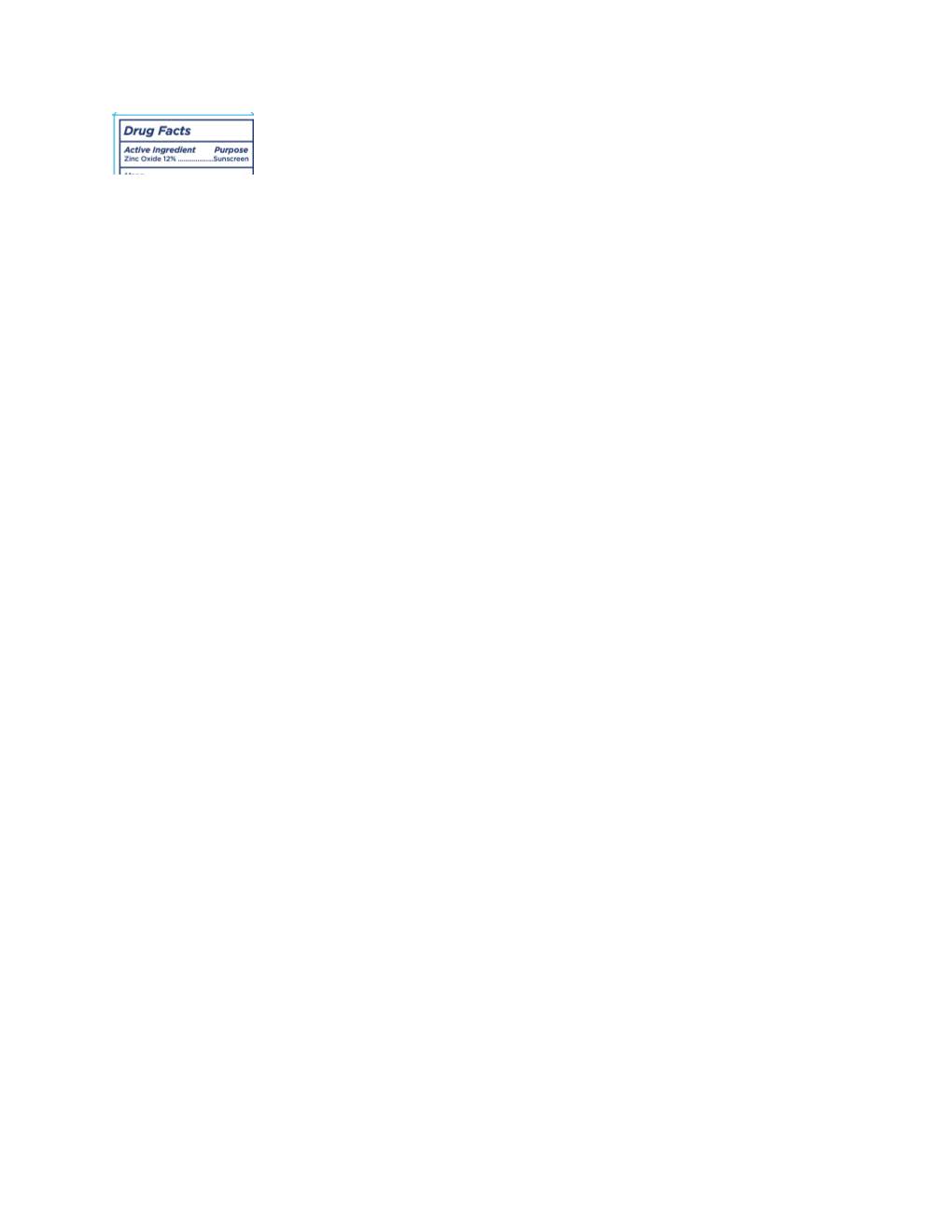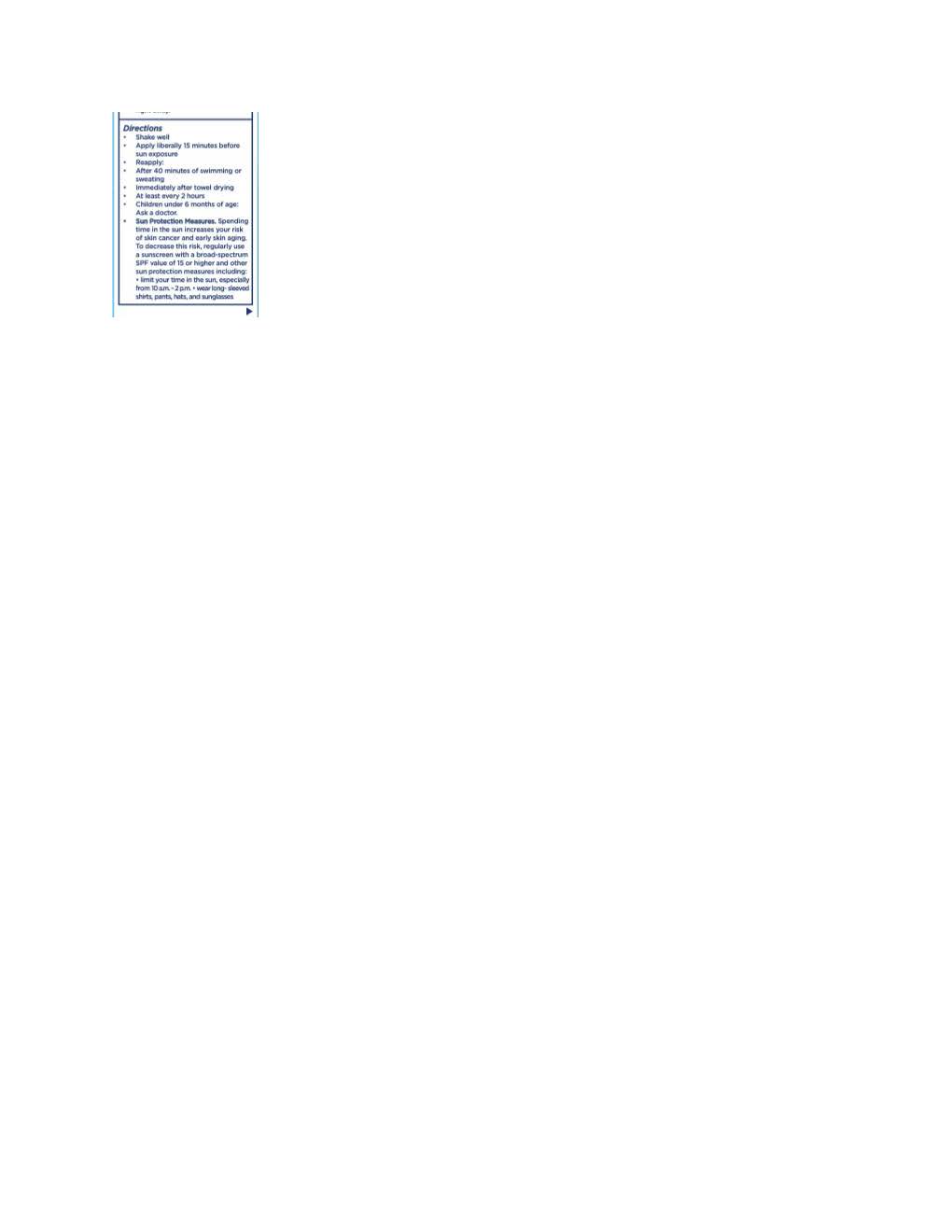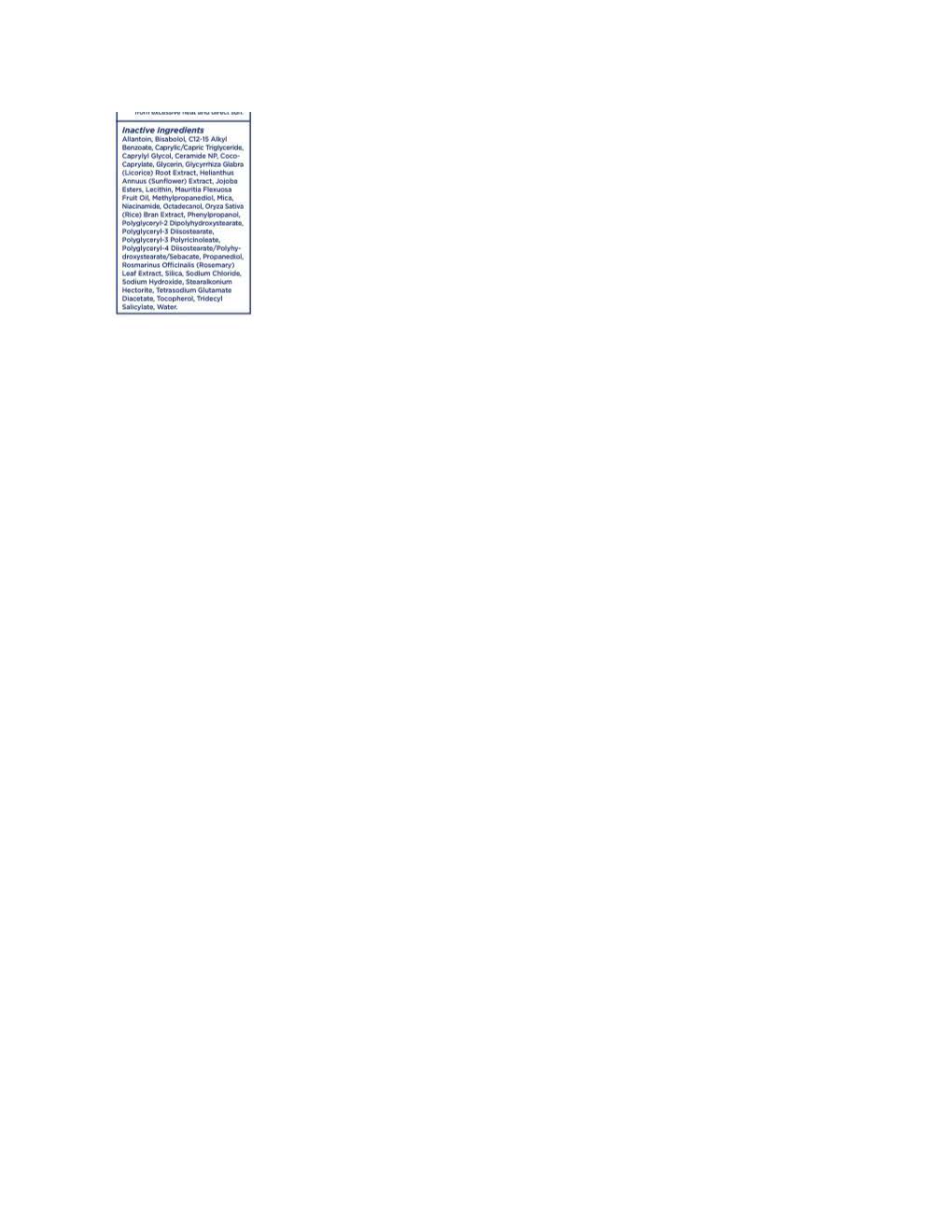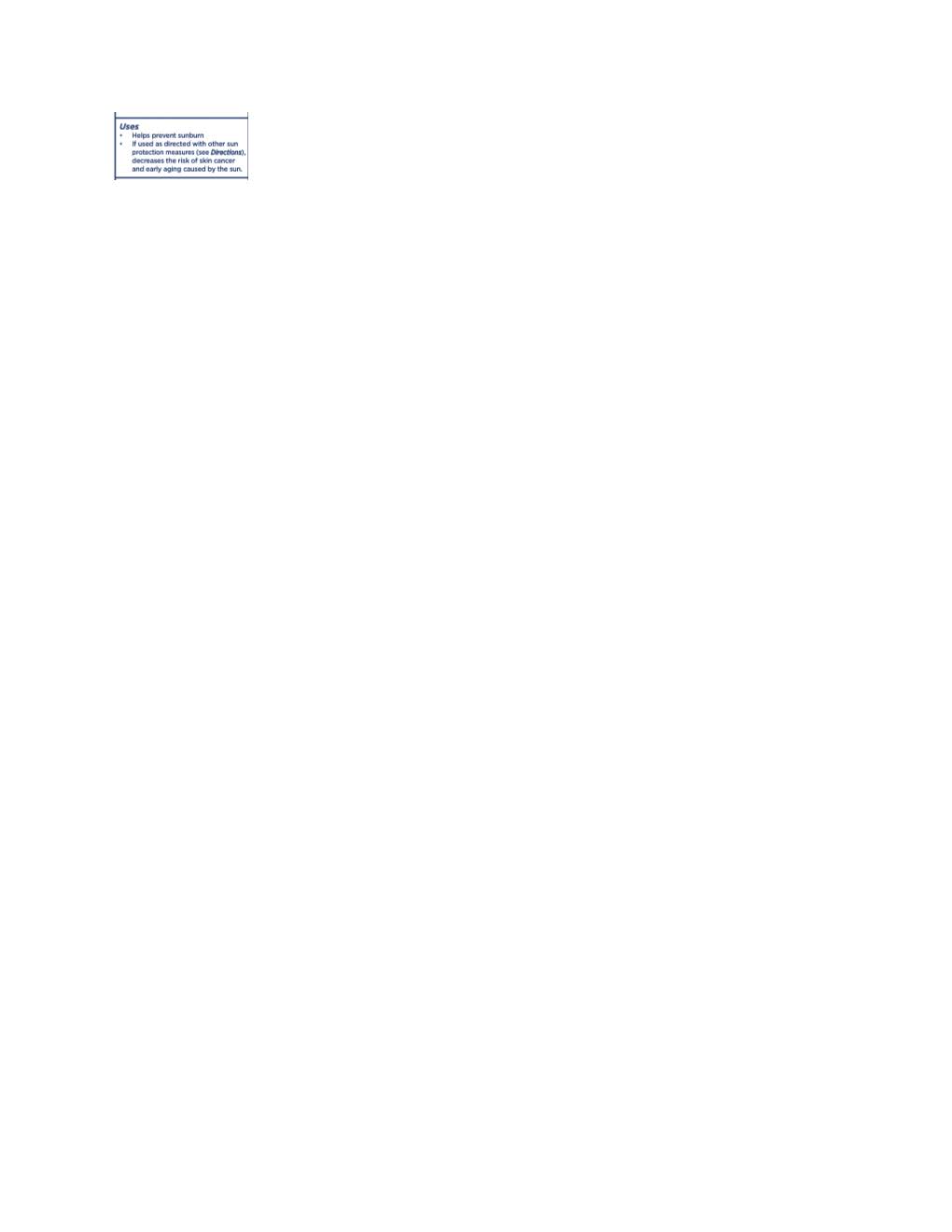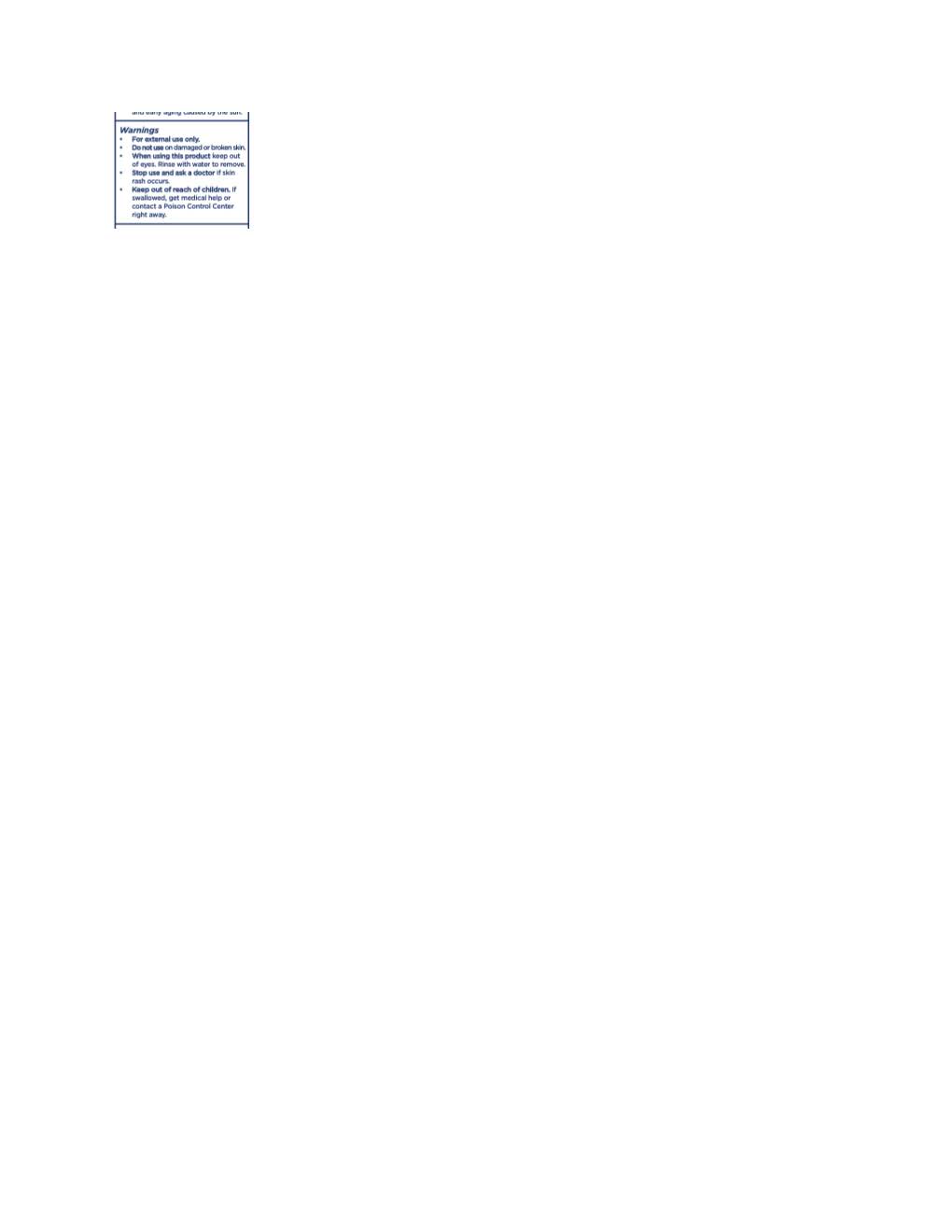 DRUG LABEL: Solar Dew Mineral Serum
NDC: 72867-2300 | Form: LOTION
Manufacturer: Tru Fragrance & Beauty LLC
Category: otc | Type: HUMAN OTC DRUG LABEL
Date: 20240823

ACTIVE INGREDIENTS: ZINC OXIDE 132 mg/1 mL
INACTIVE INGREDIENTS: MICA; CERAMIDE NP; OCTYLDODECANOL; POLYGLYCERYL-3 DIISOSTEARATE; MAURITIA FLEXUOSA FRUIT OIL; GLYCYRRHIZA GLABRA; JOJOBA OIL; ORYZA SATIVA WHOLE; TRIDECYL SALICYLATE; SILICON DIOXIDE; TOCOPHEROL; CAPRYLYL GLYCOL; COCO-CAPRYLATE; PHENYLPROPANOL; HELIANTHUS ANNUUS FLOWERING TOP; LECITHIN, SOYBEAN; METHYLPROPANEDIOL; POLYGLYCERYL-2 DIPOLYHYDROXYSTEARATE; ALLANTOIN; ALKYL (C12-15) BENZOATE; ROSMARINUS OFFICINALIS FLOWER; .ALPHA.-BISABOLOL, (+)-; SODIUM HYDROXIDE; WATER; NIACINAMIDE; PROPANEDIOL; TETRASODIUM GLUTAMATE DIACETATE; SODIUM CHLORIDE; POLYGLYCERYL-4 DIISOSTEARATE/POLYHYDROXYSTEARATE/SEBACATE; GLYCERIN; STEARALKONIUM HECTORITE

Solar Dew Mineral Serum